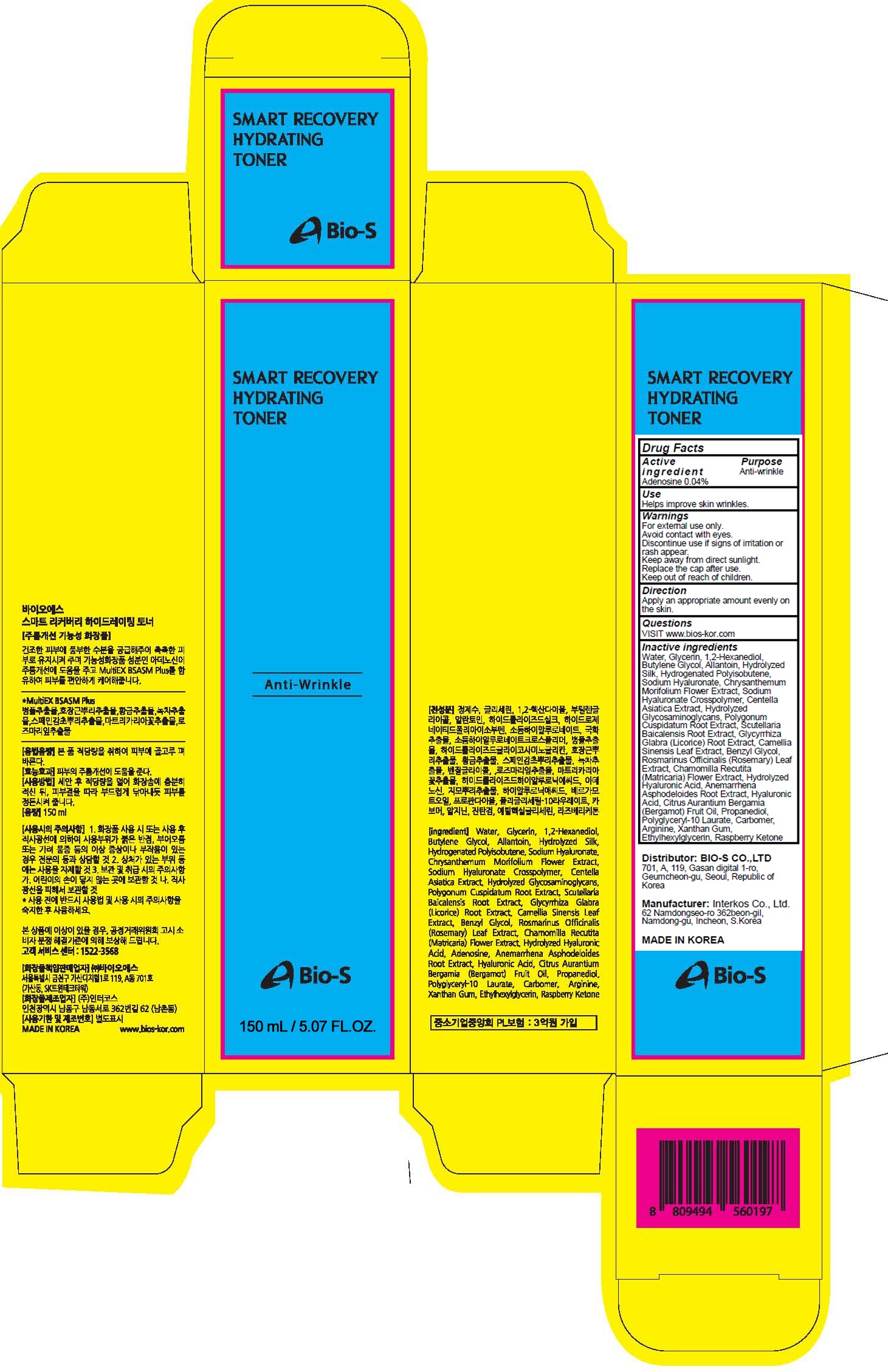 DRUG LABEL: SMART RECOVERY HYDRATING TONER
NDC: 81211-010 | Form: LIQUID
Manufacturer: BIO-S CO.,LTD
Category: otc | Type: HUMAN OTC DRUG LABEL
Date: 20201210

ACTIVE INGREDIENTS: Adenosine 0.06 g/150 mL
INACTIVE INGREDIENTS: Water; Glycerin; 1,2-Hexanediol; Butylene Glycol; Allantoin

ACTIVE INGREDIENT

Adenosine 0.04%

PURPOSE

Anti-wrinkle

Use

Helps improve skin wrinkles.

WARNINGS

For external use only.
Avoid contact with eyes.
Discontinue use if signs of irritation or rash appear.
Keep away from direct sunlight.
Replace the cap after use.
Keep out of reach of children.

KEEP OUT OF REACH OF CHILDREN

Direction

Apply an appropriate amount evenly on the skin.

QUESTIONS

VISIT www.bios-kor.com

INACTIVE INGREDIENTS

Water, Glycerin, 1,2-Hexanediol, Butylene Glycol, Allantoin, Hydrolyzed Silk, Hydrogenated Polyisobutene, Sodium Hyaluronate, Chrysanthemum Morifolium Flower Extract, Sodium Hyaluronate Crosspolymer, Centella Asiatica Extract, Hydrolyzed Glycosaminoglycans, Polygonum Cuspidatum Root Extract, Scutellaria Baicalensis Root Extract, Glycyrrhiza Glabra (Licorice) Root Extract, Camellia Sinensis Leaf Extract, Benzyl Glycol, Rosmarinus Officinalis (Rosemary) Leaf Extract, Chamomilla Recutita (Matricaria) Flower Extract, Hydrolyzed Hyaluronic Acid, Anemarrhena Asphodeloides Root Extract, Hyaluronic Acid, Citrus Aurantium Bergamia (Bergamot) Fruit Oil, Propanediol, Polyglyceryl-10 Laurate, Carbomer, Arginine, Xanthan Gum, Ethylhexylglycerin, Raspberry Ketone